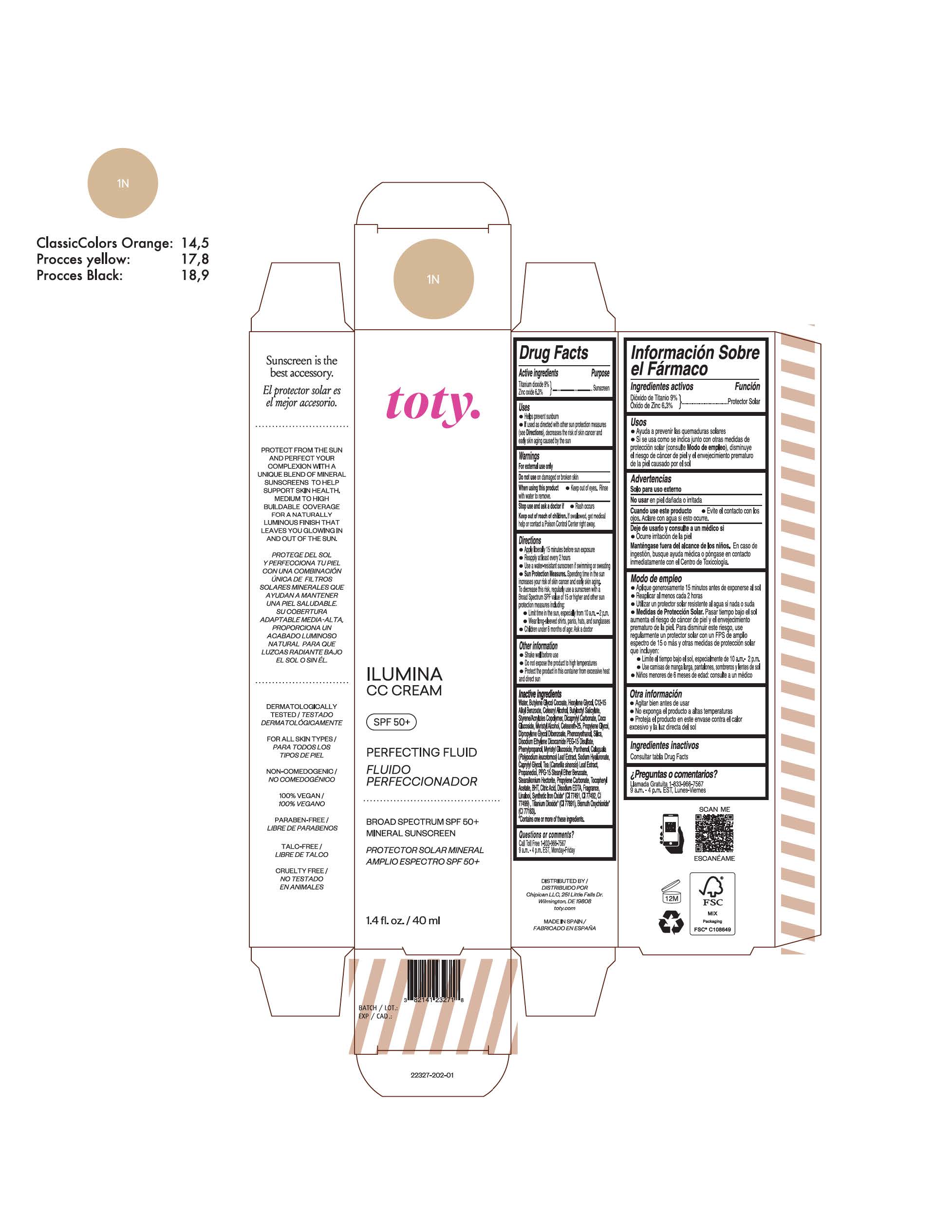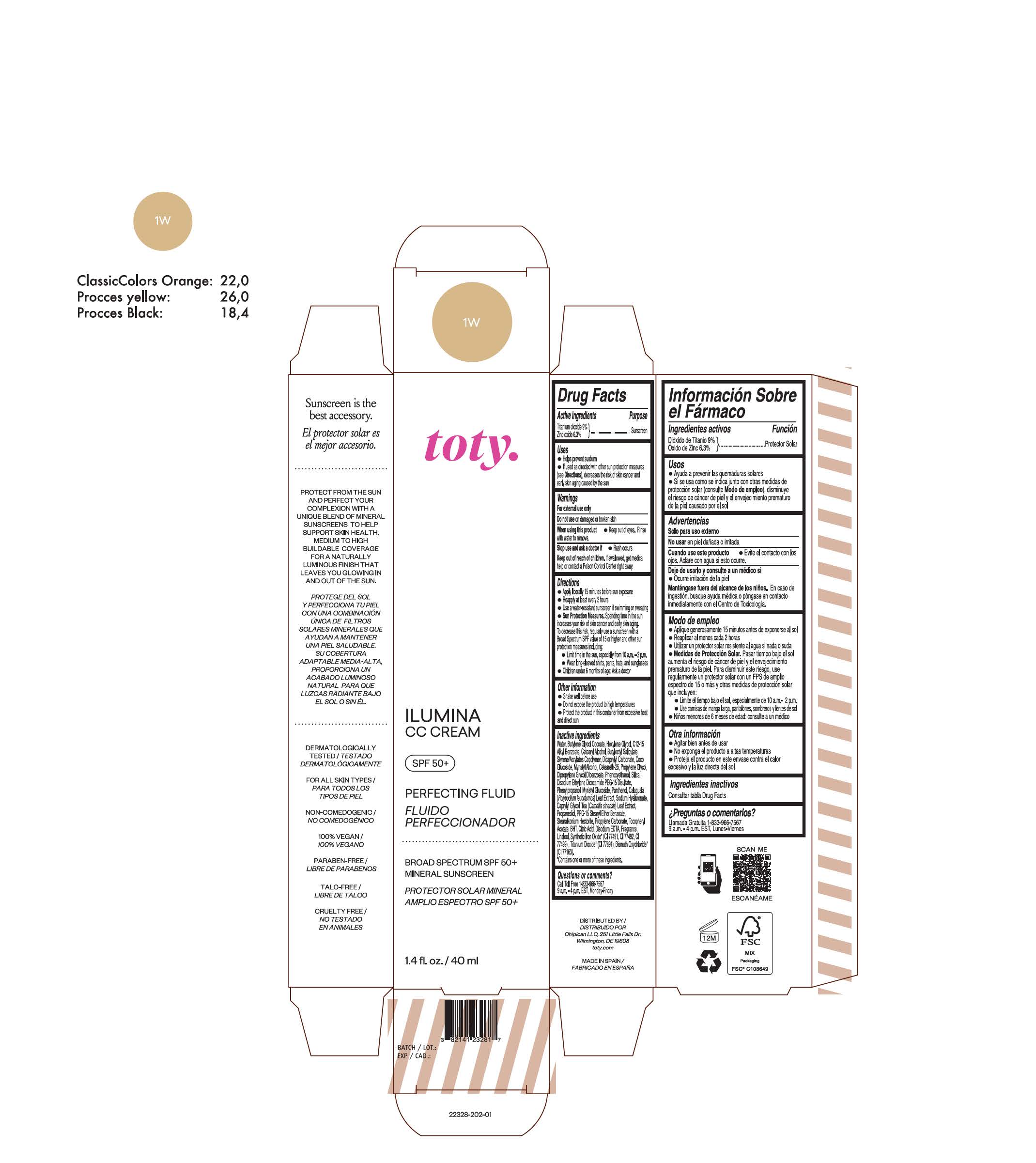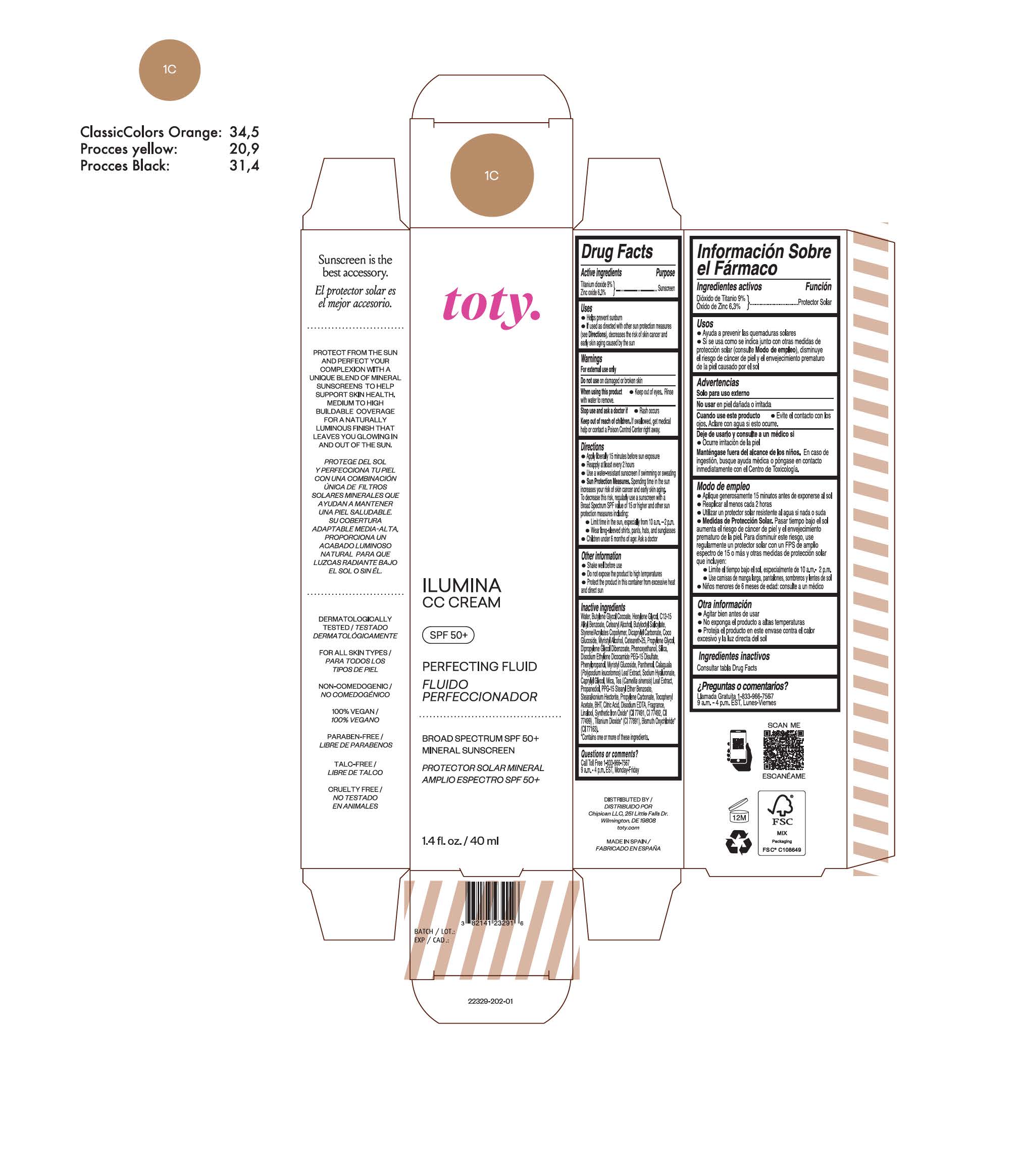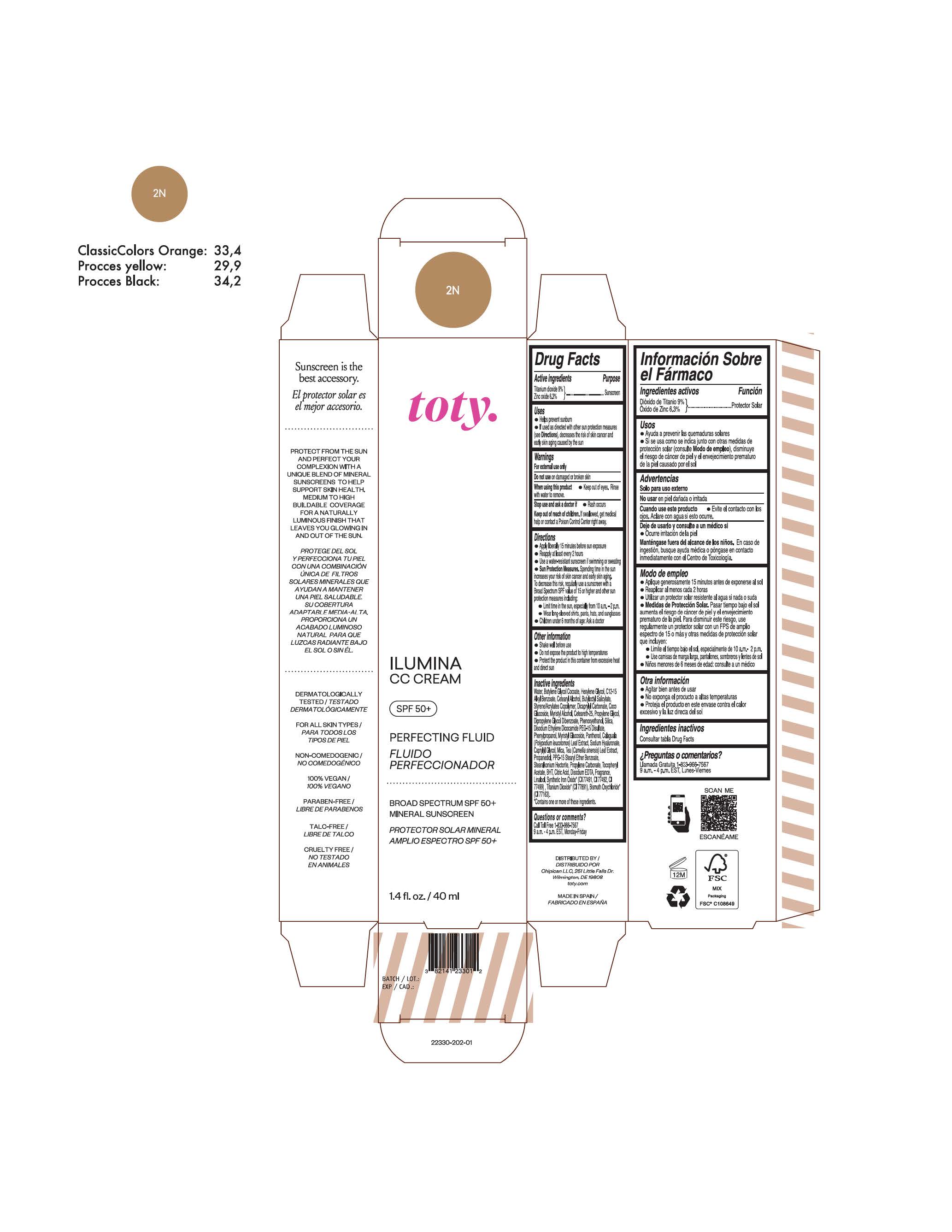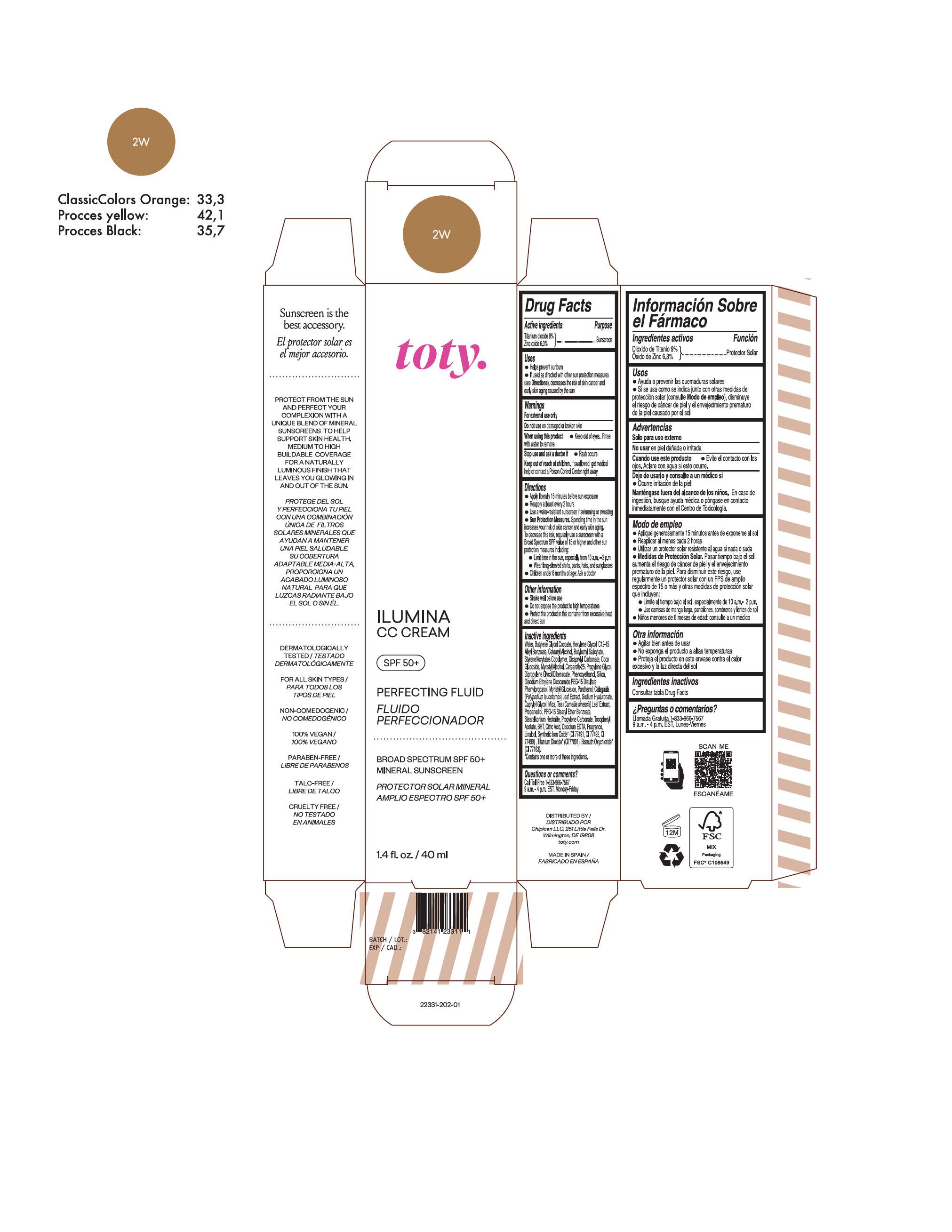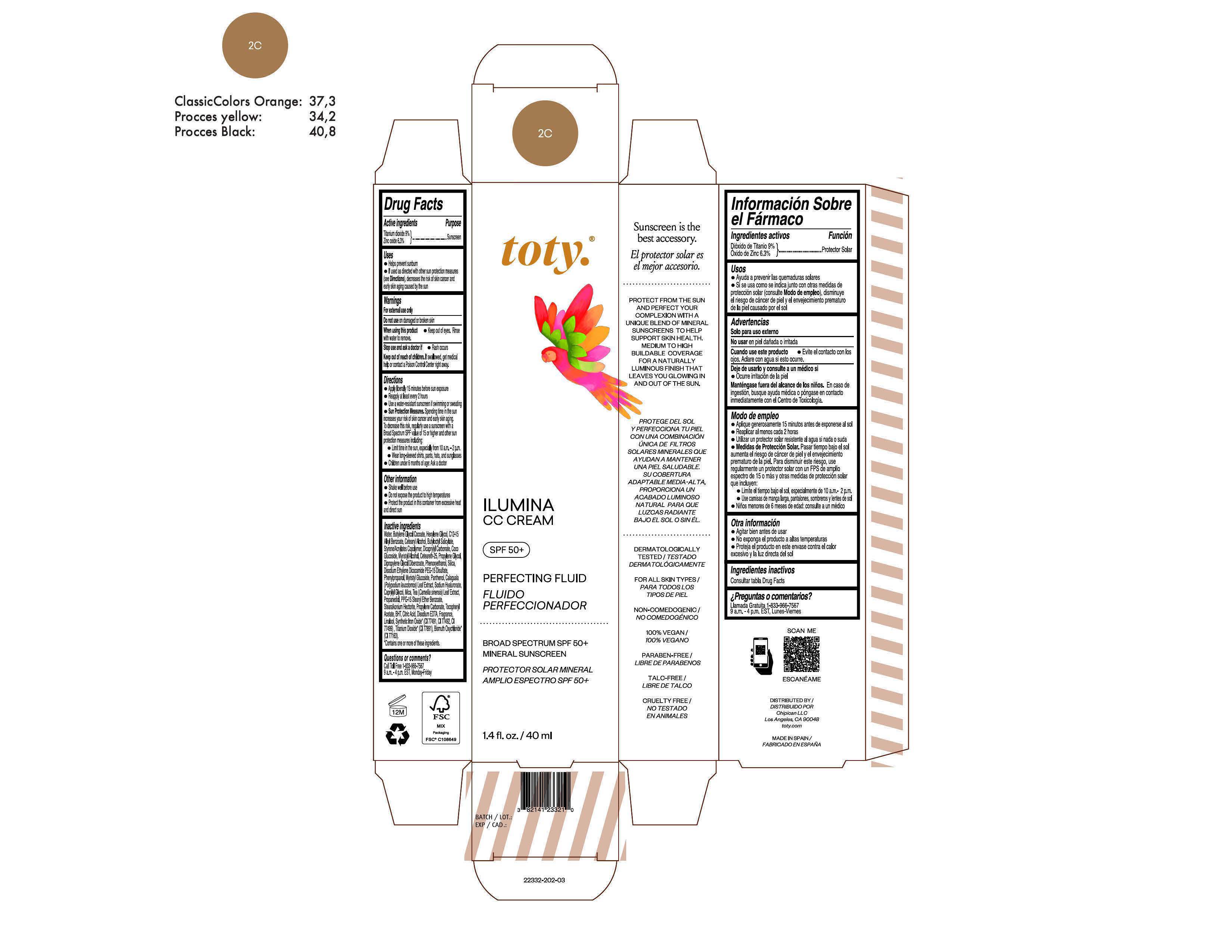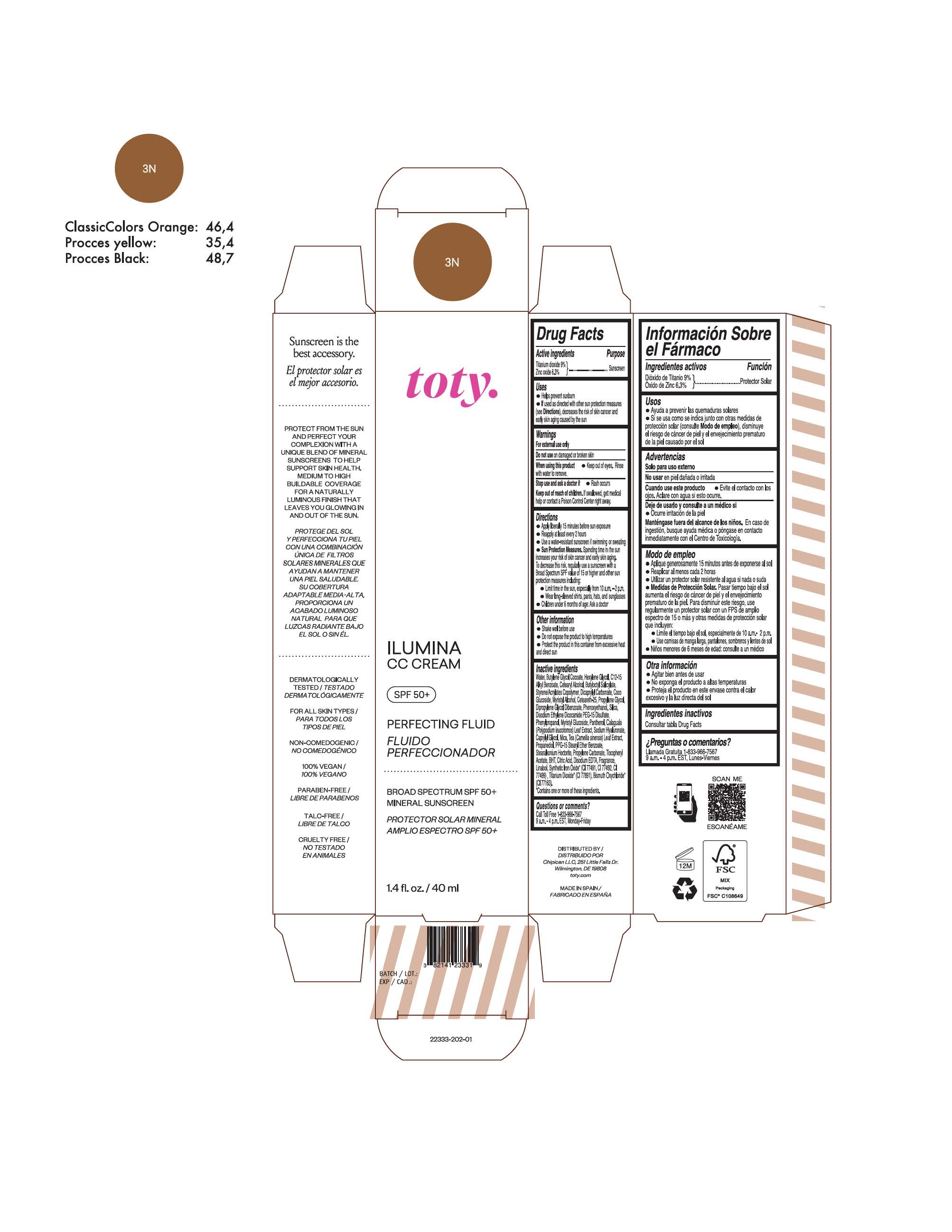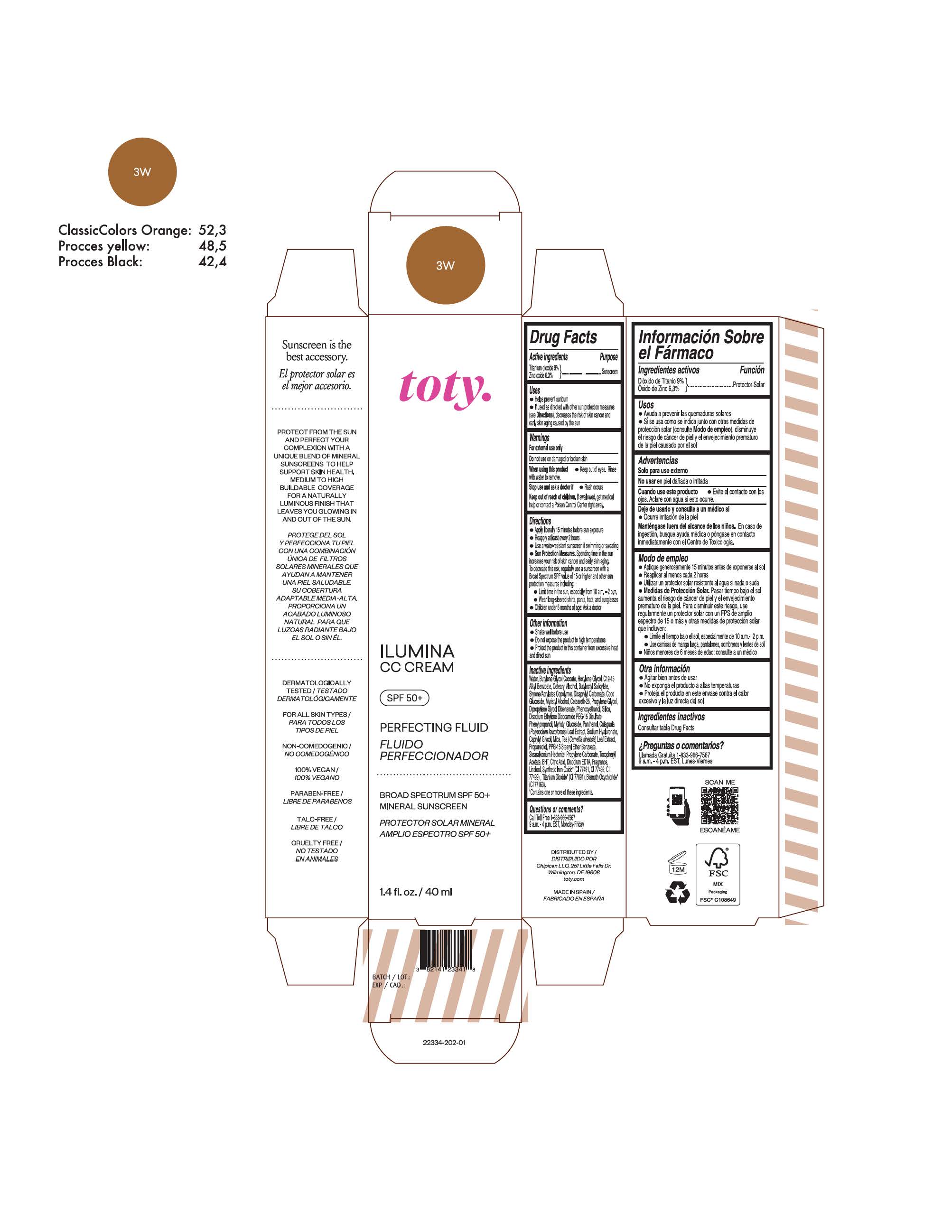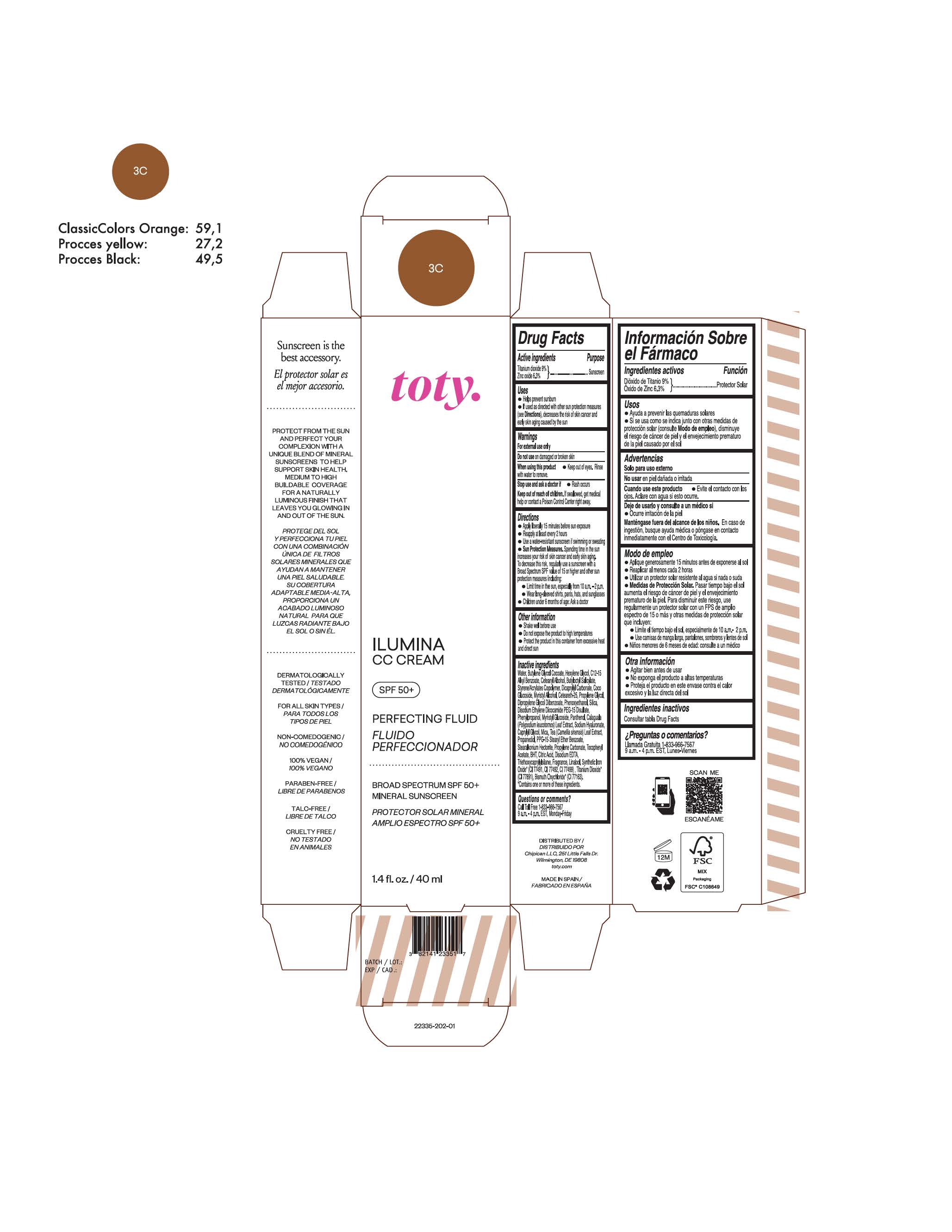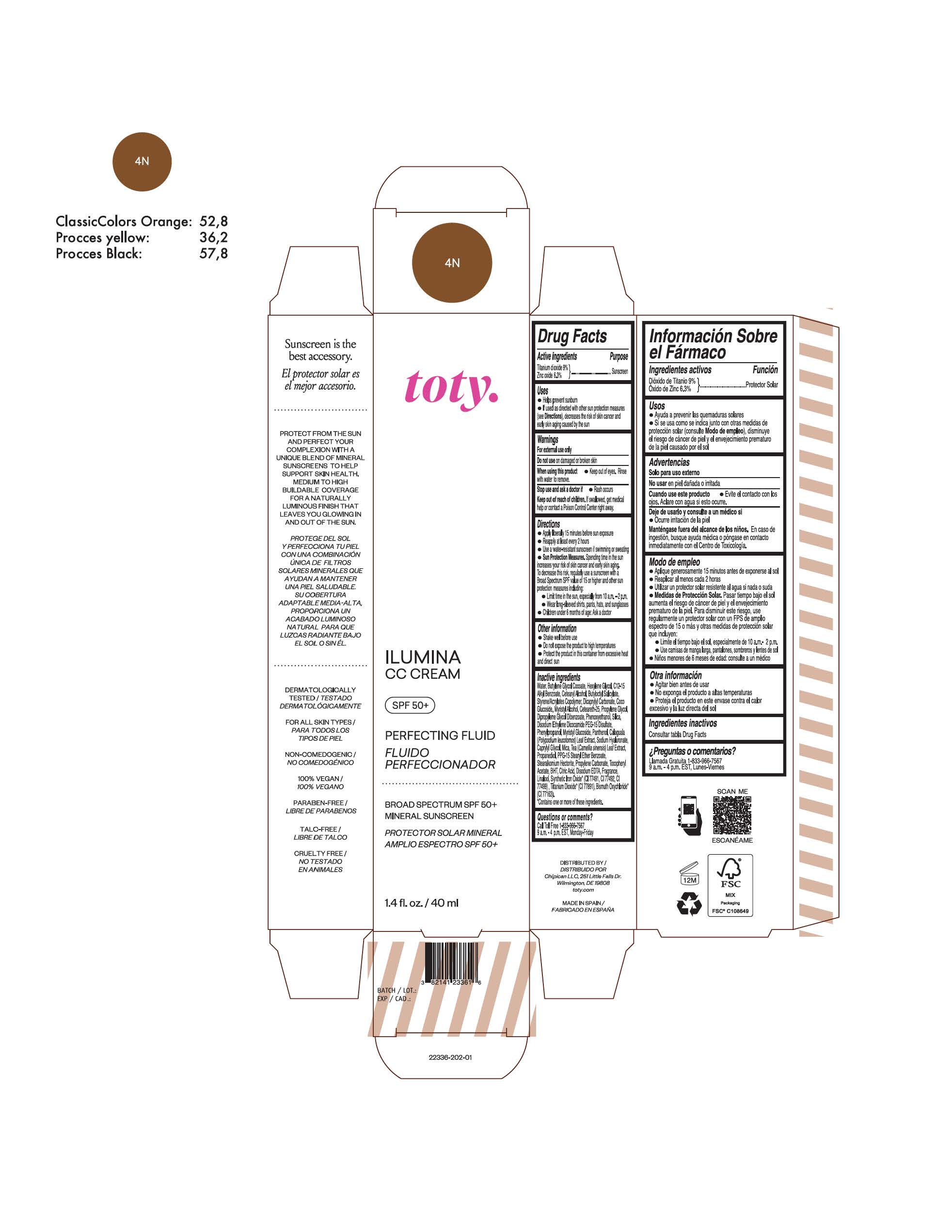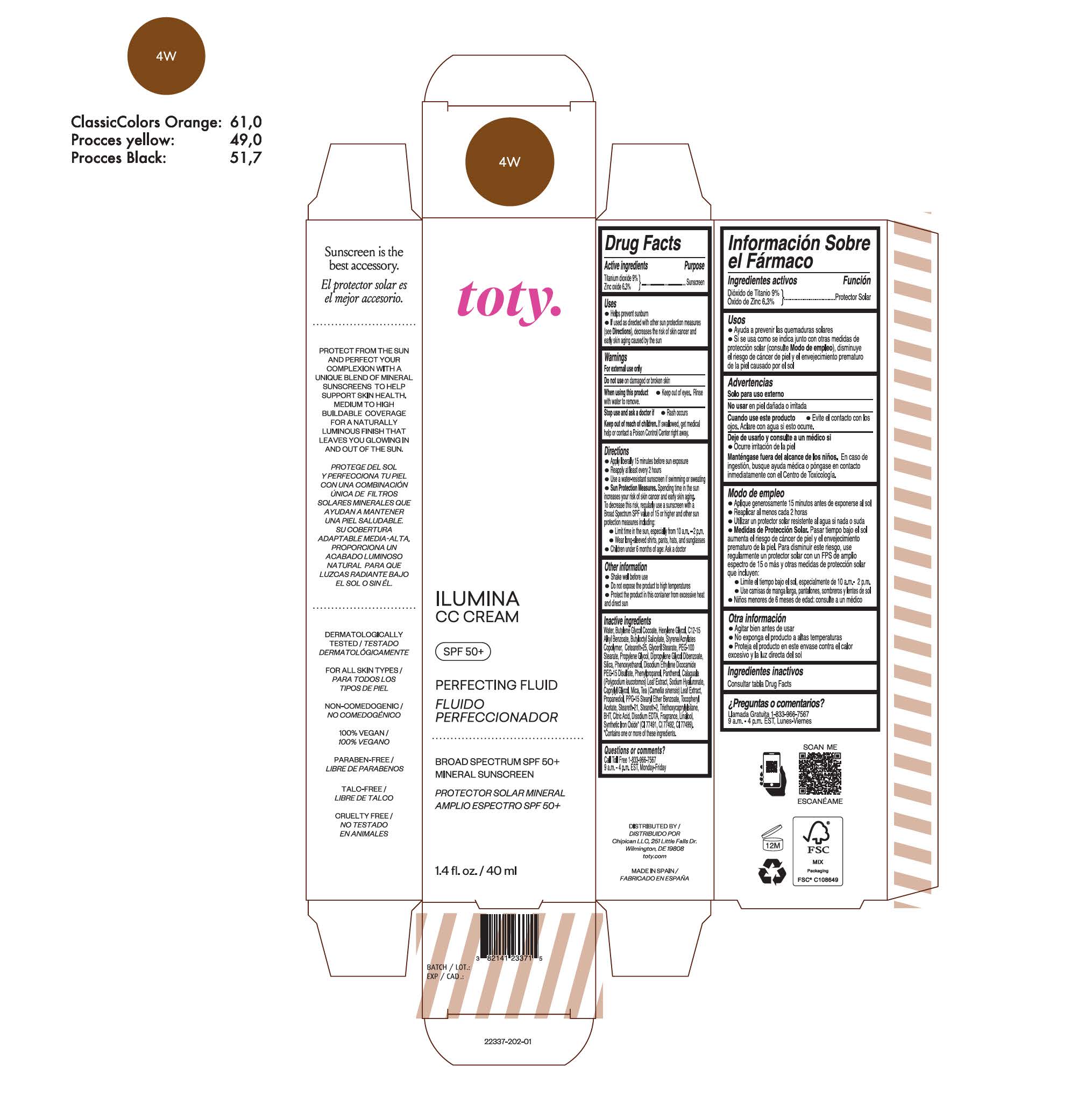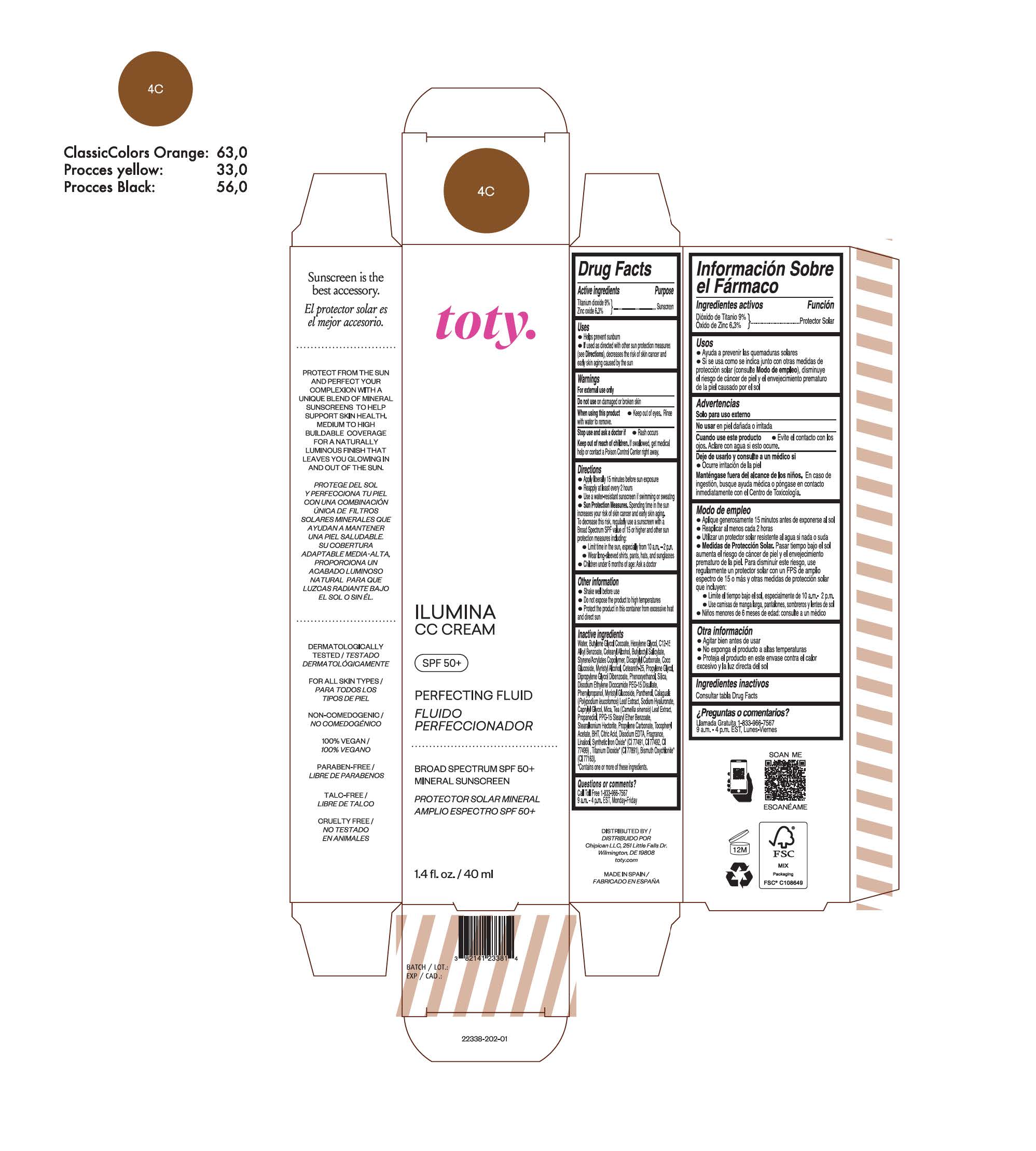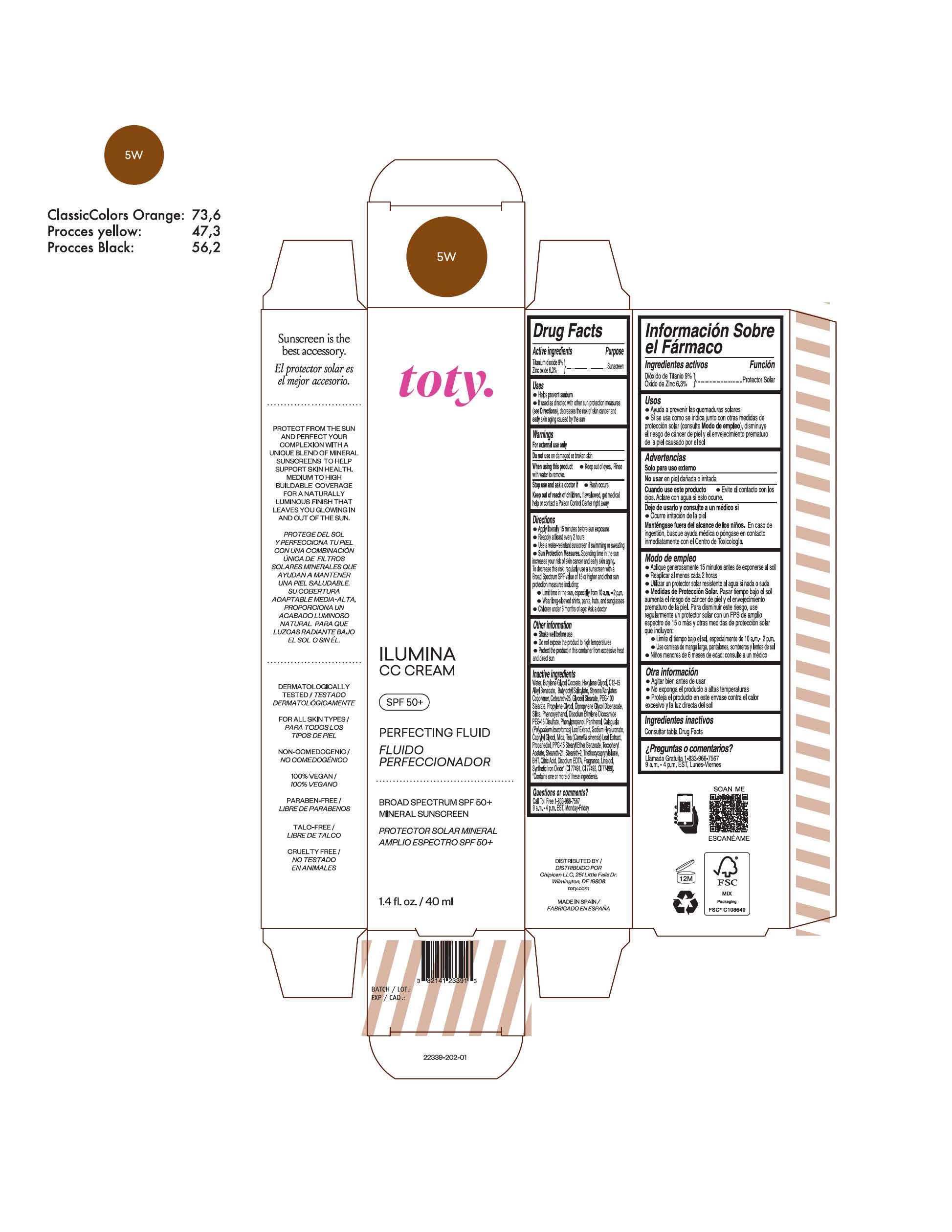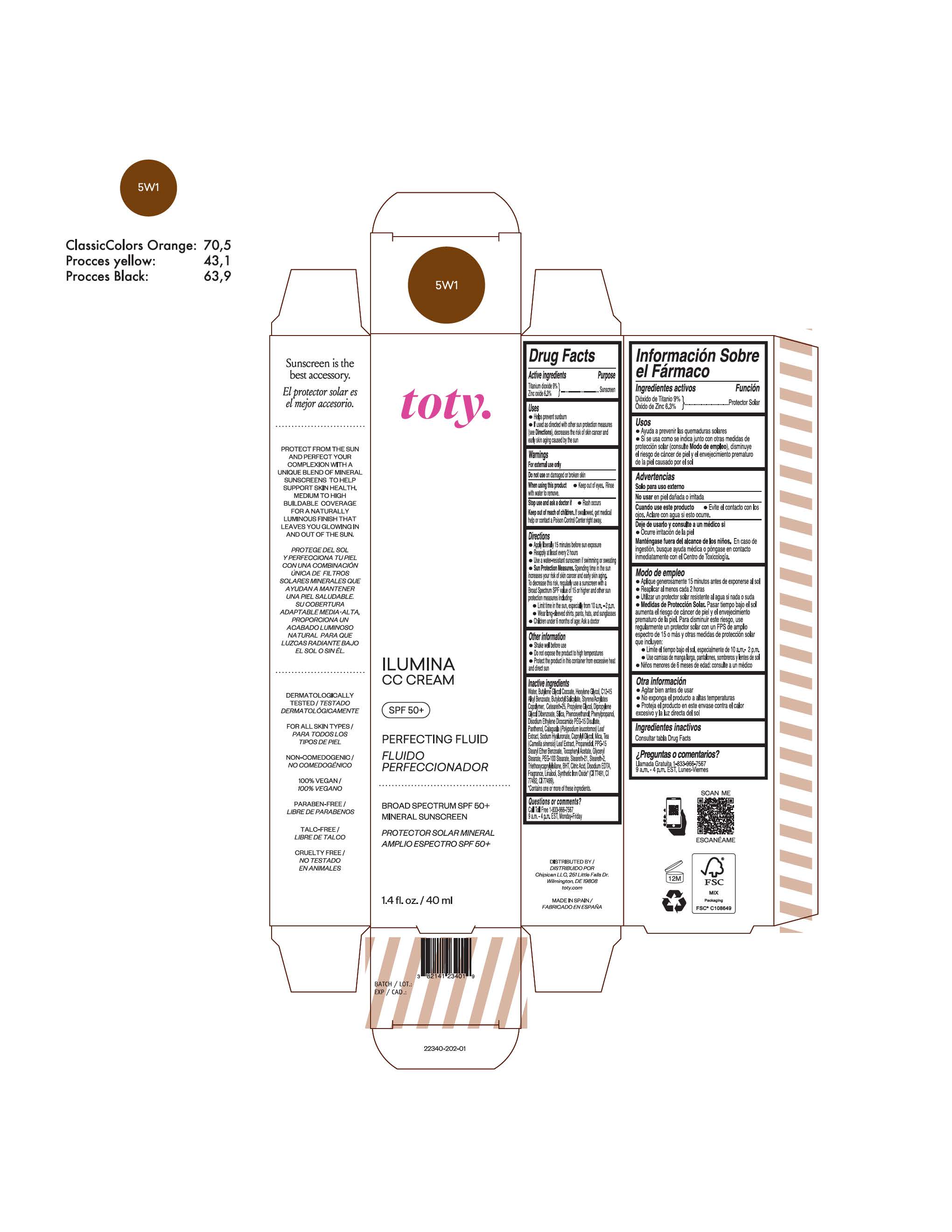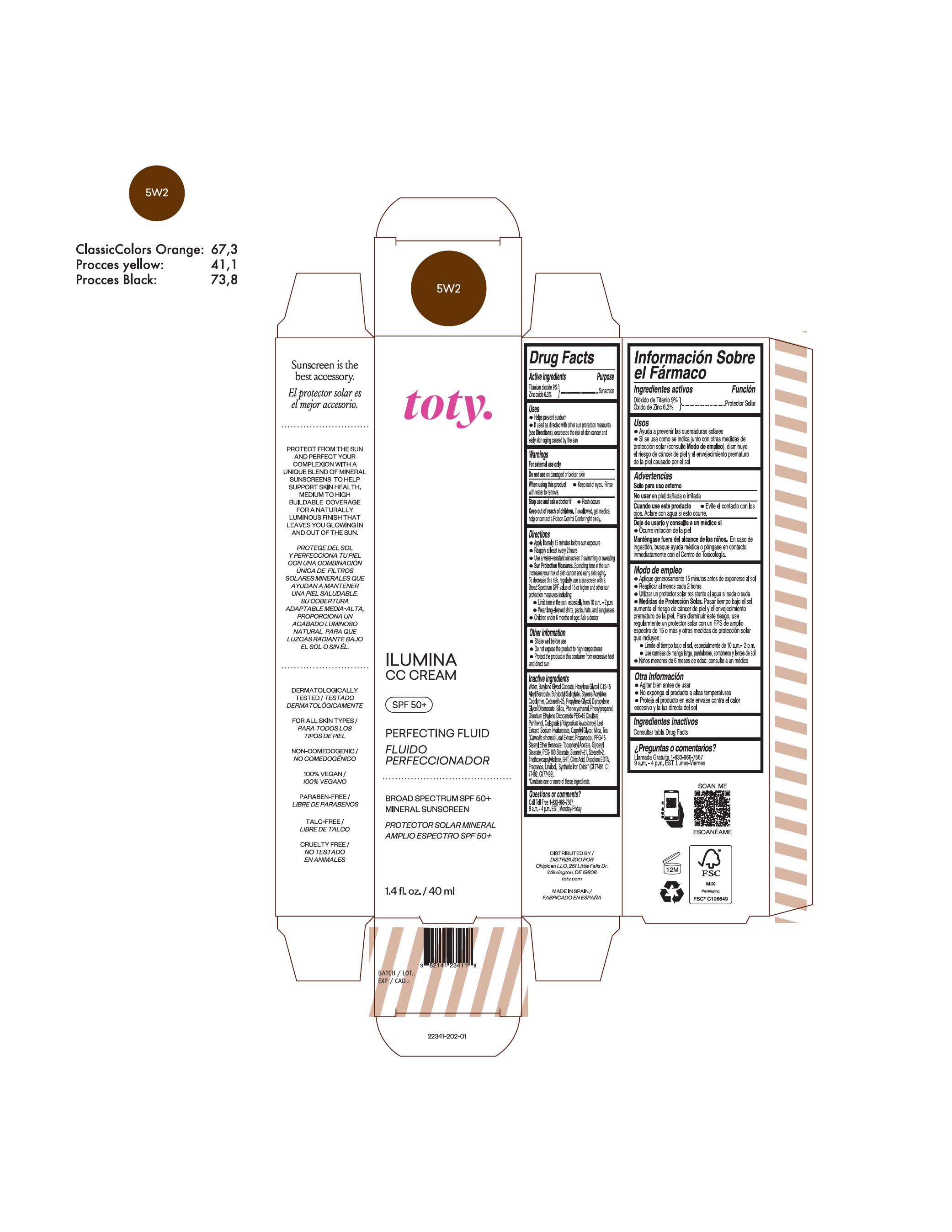 DRUG LABEL: toty Ilumina CC Cream 1N
NDC: 82141-2327 | Form: CREAM
Manufacturer: Chipican LLC
Category: otc | Type: HUMAN OTC DRUG LABEL
Date: 20241219

ACTIVE INGREDIENTS: TITANIUM DIOXIDE 9 g/100 g; ZINC OXIDE 6.3 g/100 g
INACTIVE INGREDIENTS: 1,3-BUTYLENE GLYCOL COCOATE; BUTYL METHACRYLATE/METHYL METHACRYLATE/METHACRYLIC ACID/STYRENE CROSSPOLYMER; BUTYLATED HYDROXYTOLUENE; CAPRYLYL GLYCOL; GREEN TEA LEAF; STEARALKONIUM HECTORITE; PROPYLENE CARBONATE; .ALPHA.-TOCOPHEROL ACETATE; PHLEBODIUM AUREUM LEAF; PROPYLENE GLYCOL; COCO GLUCOSIDE; WATER; HEXYLENE GLYCOL; ALKYL (C12-15) BENZOATE; CETEARETH-25; EDETATE DISODIUM ANHYDROUS; LINALOOL, (+/-)-; FERRIC OXIDE RED; FERRIC OXIDE YELLOW; HYALURONATE SODIUM; DICAPRYLYL CARBONATE; DIPROPYLENE GLYCOL DIBENZOATE; PROPANEDIOL; ANHYDROUS CITRIC ACID; CETOSTEARYL ALCOHOL; BUTYLOCTYL SALICYLATE; PHENOXYETHANOL; SILICON DIOXIDE; DISODIUM ETHYLENE DICOCAMIDE PEG-15 DISULFATE; PPG-15 STEARYL ETHER BENZOATE; PHENYLPROPANOL; MYRISTYL ALCOHOL; MYRISTYL GLUCOSIDE; PANTHENOL

toty Ilumina CC Cream

Active Ingredients

Titanium Dioxide 9%

Zinc Oxide 6.3%

Purpose

Sunscreen

Uses

- Helps prevent sunburn
- If used as directed with other sun protection measures (see Directions), decreases the risk of skin cancer and early skin aging caused by the sun.

Warnings

For external use only

Do not use on damaged or broken skin

When using this product Keep out of eyes. Rinse

with water to remove.

Stop use and ask a doctor if Rash occurs

Keep out of reach of children. If swallowed, get medical help or contact a Poison Control Center right away.

DOSAGE AND ADMINISTRATION

- Apply liberally 15 minutes behore sun exposure
- Reapply at least every 2 hours
- Use a water-resistant sunscreen if swimmimg or sweating
- Sun Protection Measures. Spending time in the sun increases your risk of skin cancer and early skin aging. To decrease this risk, regularly use a sunscreen with a Broad Spectrum SPF value of 15 or higher and other sun protection measures including:
- Limit time in the sun, especially from 10 a.m. - 2 p.m
- Wear long-sleeved shirts, pants, hats, and sunglasses
- Children under 6 months of age: Ask a doctor.

Other Information

- Shake well before use
- Do not expose the product to high temperatures
- Protect the product in this container from excessive heat and direct sun

Inactive Ingredients

NDCs 82141-2327-1, 82141-2328-1

Water, Butylene Glycol Cocoate,Hexylene Glycol, C12-15

Alkyl Benzoate, Cetearyl Alcohol, Butyloctyl Salicylate,

Styrene/Acrylates Copolymer, Dicaprylyl Carbonate, Coco

Glucoside, Myristyl Alcohol, Ceteareth-25, Propylene Glycol,

Dipropylene Glycol Dibenzoate, Phenoxyethanol, Silica,

Disodium Ethylene Dicocamide PEG-15 Disulfate,

Phenylpropanol, Myristyl Glucoside, Panthenol, Calaguala

(Polypodium leucotomos) Leaf Extract, Sodium Hyaluronate,

Caprylyl Glycol, Tea (Camellia sinensis) Leaf Extract,

Propanediol, PPG-15 Stearyl Ether Benzoate,

Stearalkonium Hectorite, Propylene Carbonate, Tocopheryl

Acetate, BHT, Citric Acid, Disodium EDTA, Fragrance,

Linalool, Synthetic Iron Oxide* (CI 77491, CI 77492, CI

77499), Titanium Dioxide* (CI 77891), Bismuth Oxychloride*

(CI 77163).

* Contains one or more of these ingredients.

NDCs 82141-2329-1, 82141-2330-1, 82141-2331-1, 82141-2332-1, 82141-2333-1

82141-2334-1, 82141-2336-1 & 82141-2338-1

Water, Butylene Glycol Cocoate,Hexylene Glycol, C12-15

Alkyl Benzoate, Cetearyl Alcohol, Butyloctyl Salicylate,

Styrene/Acrylates Copolymer, Dicaprylyl Carbonate, Coco

Glucoside, Myristyl Alcohol, Ceteareth-25, Propylene Glycol,

Dipropylene Glycol Dibenzoate, Phenoxyethanol, Silica,

Disodium Ethylene Dicocamide PEG-15 Disulfate,

Phenylpropanol, Myristyl Glucoside, Panthenol, Calaguala

(Polypodium leucotomos) Leaf Extract, Sodium Hyaluronate,

Caprylyl Glycol, Mica, Tea (Camellia sinensis) Leaf Extract,

Propanediol, PPG-15 Stearyl Ether Benzoate,

Stearalkonium Hectorite, Propylene Carbonate, Tocopheryl

Acetate, BHT, Citric Acid, Disodium EDTA, Fragrance,

Linalool, Synthetic Iron Oxide* (CI 77491, CI 77492, CI

77499), Titanium Dioxide* (CI 77891), Bismuth Oxychloride*

(CI 77163).

* Contains one or more of these ingredients.

NDCs 82141-2335-1

Water, Butylene Glycol Cocoate,Hexylene Glycol, C12-15

Alkyl Benzoate, Cetearyl Alcohol, Butyloctyl Salicylate,

Styrene/Acrylates Copolymer, Dicaprylyl Carbonate, Coco

Glucoside, Myristyl Alcohol, Ceteareth-25, Propylene Glycol,

Dipropylene Glycol Dibenzoate, Phenoxyethanol, Silica,

Disodium Ethylene Dicocamide PEG-15 Disulfate,

Phenylpropanol, Myristyl Glucoside, Panthenol, Calaguala

(Polypodium leucotomos) Leaf Extract, Sodium Hyaluronate,

Caprylyl Glycol, Mica, Tea (Camellia sinensis) Leaf Extract,

Propanediol, PPG-15 Stearyl Ether Benzoate,

Stearalkonium Hectorite, Propylene Carbonate, Tocopheryl

Acetate, BHT, Citric Acid, Disodium EDTA,

Triethoxycaprylylsilane, Fragrance, Linalool, Synthetic Iron

Oxide* (CI 77491, CI 77492, CI 77499), Titanium Dioxide*

(CI 77891), Bismuth Oxychloride* (CI 77163).

* Contains one or more of these ingredients.

NDCs 82141-2337-1 &82141-2339-1

Water, Butylene Glycol Cocoate,Hexylene Glycol, C12-15

Alkyl Benzoate, Butyloctyl Salicylate, Styrene/Acrylates

Copolymer, Ceteareth-25, Glyceril Stearate, PEG-100

Stearate, Propylene Glycol, Dipropylene Glycol Dibenzoate,

Silica, Phenoxyethanol, Disodium Ethylene Dicocamide

PEG-15 Disulfate, Phenylpropanol, Panthenol, Calaguala

(Polypodium leucotomos) Leaf Extract, Sodium Hyaluronate,

Caprylyl Glycol, Mica, Tea (Camellia sinensis) Leaf Extract,

Propanediol, PPG-15 Stearyl Ether Benzoate, Tocopheryl

Acetate, Steareth-21, Steareth-2, Triethoxycaprylylsilane,

BHT, Citric Acid, Disodium EDTA, Fragrance, Linalool,

Synthetic Iron Oxide* (CI 77491, CI 77492, CI 77499).

* Contains one or more of these ingredients.

NDCs 82141-2340-1 & 82141-2341-1

Water, Butylene Glycol Cocoate,Hexylene Glycol, C12-15

Alkyl Benzoate, Butyloctyl Salicylate, Styrene/Acrylates

Copolymer, Ceteareth-25, Propylene Glycol, Dipropylene

Glycol Dibenzoate, Silica, Phenoxyethanol, Phenylpropanol,

Disodium Ethylene Dicocamide PEG-15 Disulfate,

Panthenol, Calaguala (Polypodium leucotomos) Leaf

Extract, Sodium Hyaluronate, Caprylyl Glycol, Mica, Tea

(Camellia sinensis) Leaf Extract, Propanediol, PPG-15

Stearyl Ether Benzoate, Tocopheryl Acetate, Glyceryl

Stearate, PEG-100 Stearate, Steareth-21, Steareth-2,

Triethoxycaprylylsilane, BHT, Citric Acid, Disodium EDTA,

Fragrance, Linalool, Synthetic Iron Oxide* (CI 77491, CI

77492, CI 77499).

* Contains one or more of these ingredients.

toty Ilumina CC Cream 1N

NDC 82141-2327-1 (toty Ilumina CC Cream 1N)

toty.

ILUMINA

CC CREAM

SPF 50+

Perfecting Fluid

Fluido

Perfeccionador

.......................................................

BROAD SPECTRUM SPF 50+

MINERAL SUNSCREEN

PROTECTOR SOLAR MINERAL

AMPLIO ESPECTRO SPF 50+

1.4 fl. oz./ 40 ml

toty Ilumina CC Cream 1W

NDC 82141-2328-1 (toty Ilumina CC Cream 1W)

toty.

ILUMINA

CC CREAM

SPF 50+

Perfecting Fluid

Fluido

Perfeccionador

.......................................................

BROAD SPECTRUM SPF 50+

MINERAL SUNSCREEN

PROTECTOR SOLAR MINERAL

AMPLIO ESPECTRO SPF 50+

1.4 fl. oz./ 40 ml

toty Ilumina CC Cream 1C

NDC 82141-2329-1 (toty Ilumina CC Cream 1C)

toty.

ILUMINA

CC CREAM

SPF 50+

Perfecting Fluid

Fluido

Perfeccionador

.......................................................

BROAD SPECTRUM SPF 50+

MINERAL SUNSCREEN

PROTECTOR SOLAR MINERAL

AMPLIO ESPECTRO SPF 50+

1.4 fl. oz./ 40 ml

toty Ilumina CC Cream 2N

NDC 82141-2330-1 (toty Ilumina CC Cream 2N)

toty.

ILUMINA

CC CREAM

SPF 50+

Perfecting Fluid

Fluido

Perfeccionador

.......................................................

BROAD SPECTRUM SPF 50+

MINERAL SUNSCREEN

PROTECTOR SOLAR MINERAL

AMPLIO ESPECTRO SPF 50+

1.4 fl. oz./ 40 ml

toty Ilumina CC Cream 2W

NDC 82141-2331-1 (toty Ilumina CC Cream 2W)

toty.

ILUMINA

CC CREAM

SPF 50+

Perfecting Fluid

Fluido

Perfeccionador

.......................................................

BROAD SPECTRUM SPF 50+

MINERAL SUNSCREEN

PROTECTOR SOLAR MINERAL

AMPLIO ESPECTRO SPF 50+

1.4 fl. oz./ 40 ml

toty Ilumina CC Cream 2C

NDC 82141-2332-1 (toty Ilumina CC Cream 2C)

toty.

ILUMINA

CC CREAM

SPF 50+

Perfecting Fluid

Fluido

Perfeccionador

.......................................................

BROAD SPECTRUM SPF 50+

MINERAL SUNSCREEN

PROTECTOR SOLAR MINERAL

AMPLIO ESPECTRO SPF 50+

1.4 fl. oz./ 40 ml

toty Ilumina CC Cream 3N

NDC 82141-2333-1 (toty Ilumina CC Cream 3N)

toty.

ILUMINA

CC CREAM

SPF 50+

Perfecting Fluid

Fluido

Perfeccionador

.......................................................

BROAD SPECTRUM SPF 50+

MINERAL SUNSCREEN

PROTECTOR SOLAR MINERAL

AMPLIO ESPECTRO SPF 50+

1.4 fl. oz./ 40 ml

toty Ilumina CC Cream 3W

NDC 82141-2334-1 (toty Ilumina CC Cream 3W)

toty.

ILUMINA

CC CREAM

SPF 50+

Perfecting Fluid

Fluido

Perfeccionador

.......................................................

BROAD SPECTRUM SPF 50+

MINERAL SUNSCREEN

PROTECTOR SOLAR MINERAL

AMPLIO ESPECTRO SPF 50+

1.4 fl. oz./ 40 ml

toty Ilumina CC Cream 3C

NDC 82141-2335-1 (toty Ilumina CC Cream 3C)

toty.

ILUMINA

CC CREAM

SPF 50+

Perfecting Fluid

Fluido

Perfeccionador

.......................................................

BROAD SPECTRUM SPF 50+

MINERAL SUNSCREEN

PROTECTOR SOLAR MINERAL

AMPLIO ESPECTRO SPF 50+

1.4 fl. oz./ 40 ml

toty Ilumina CC Cream 4N

NDC 82141-2336-1 (toty Ilumina CC Cream 4N)

toty.

ILUMINA

CC CREAM

SPF 50+

Perfecting Fluid

Fluido

Perfeccionador

.......................................................

BROAD SPECTRUM SPF 50+

MINERAL SUNSCREEN

PROTECTOR SOLAR MINERAL

AMPLIO ESPECTRO SPF 50+

1.4 fl. oz./ 40 ml

toty Ilumina CC Cream 4W

NDC 82141-2337-1 (toty Ilumina CC Cream 4W)

toty.

ILUMINA

CC CREAM

SPF 50+

Perfecting Fluid

Fluido

Perfeccionador

.......................................................

BROAD SPECTRUM SPF 50+

MINERAL SUNSCREEN

PROTECTOR SOLAR MINERAL

AMPLIO ESPECTRO SPF 50+

1.4 fl. oz./ 40 ml

toty Ilumina CC Cream 4C

NDC 82141-2338-1 (toty Ilumina CC Cream 4C)

toty.

ILUMINA

CC CREAM

SPF 50+

Perfecting Fluid

Fluido

Perfeccionador

.......................................................

BROAD SPECTRUM SPF 50+

MINERAL SUNSCREEN

PROTECTOR SOLAR MINERAL

AMPLIO ESPECTRO SPF 50+

1.4 fl. oz./ 40 ml

toty Ilumina CC Cream 5W

NDC 82141-2339-1 (toty Ilumina CC Cream 5W)

toty.

ILUMINA

CC CREAM

SPF 50+

Perfecting Fluid

Fluido

Perfeccionador

.......................................................

BROAD SPECTRUM SPF 50+

MINERAL SUNSCREEN

PROTECTOR SOLAR MINERAL

AMPLIO ESPECTRO SPF 50+

1.4 fl. oz./ 40 ml

toty Ilumina CC Cream 5W1

NDC 82141-2340-1 (toty Ilumina CC Cream 5W1)

toty.

ILUMINA

CC CREAM

SPF 50+

Perfecting Fluid

Fluido

Perfeccionador

.......................................................

BROAD SPECTRUM SPF 50+

MINERAL SUNSCREEN

PROTECTOR SOLAR MINERAL

AMPLIO ESPECTRO SPF 50+

1.4 fl. oz./ 40 ml

toty Ilumina CC Cream 5W2

NDC 82141-2341-1 (toty Ilumina CC Cream 5W2)

toty.

ILUMINA

CC CREAM

SPF 50+

Perfecting Fluid

Fluido

Perfeccionador

.......................................................

BROAD SPECTRUM SPF 50+

MINERAL SUNSCREEN

PROTECTOR SOLAR MINERAL

AMPLIO ESPECTRO SPF 50+

1.4 fl. oz./ 40 ml